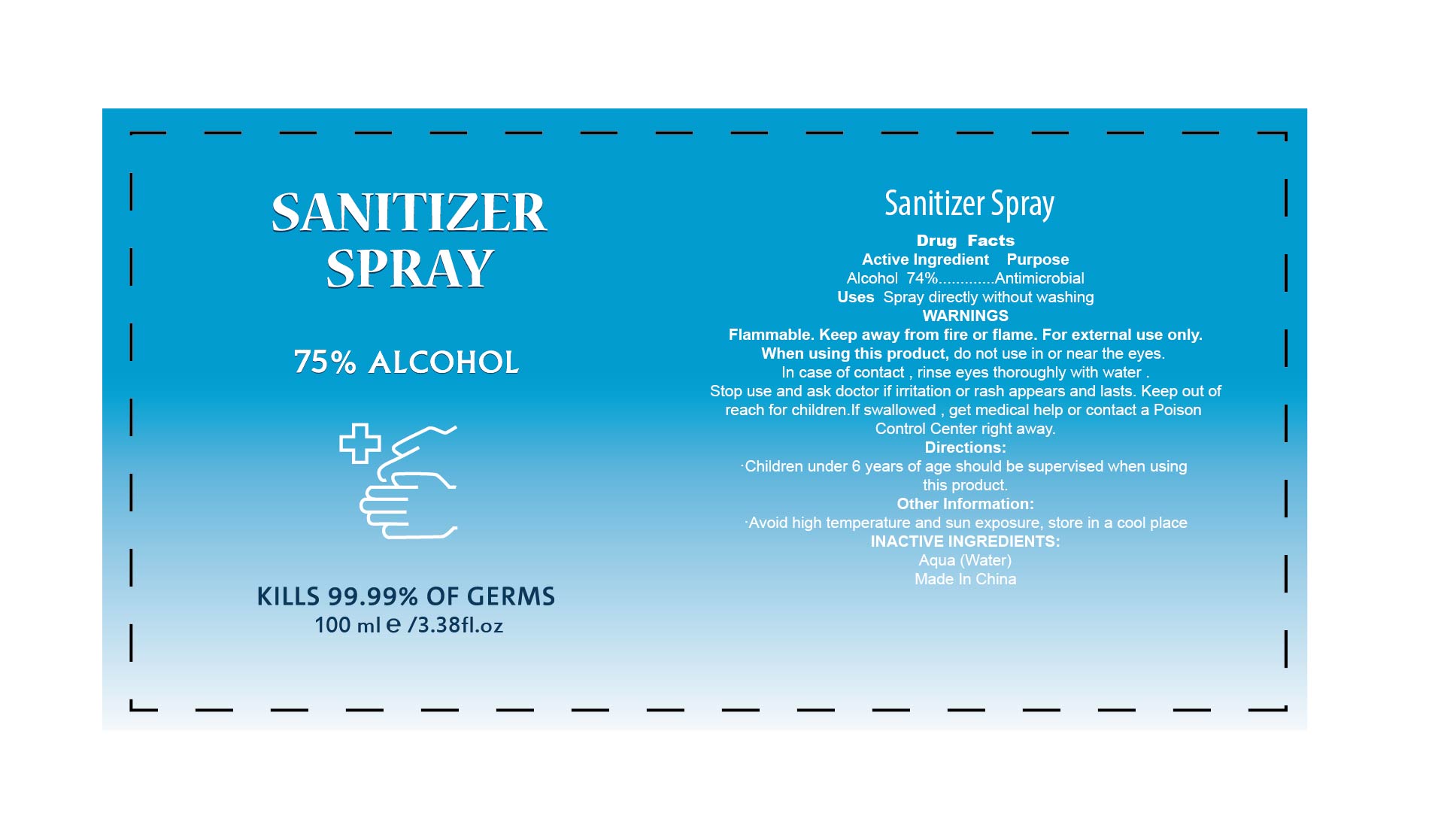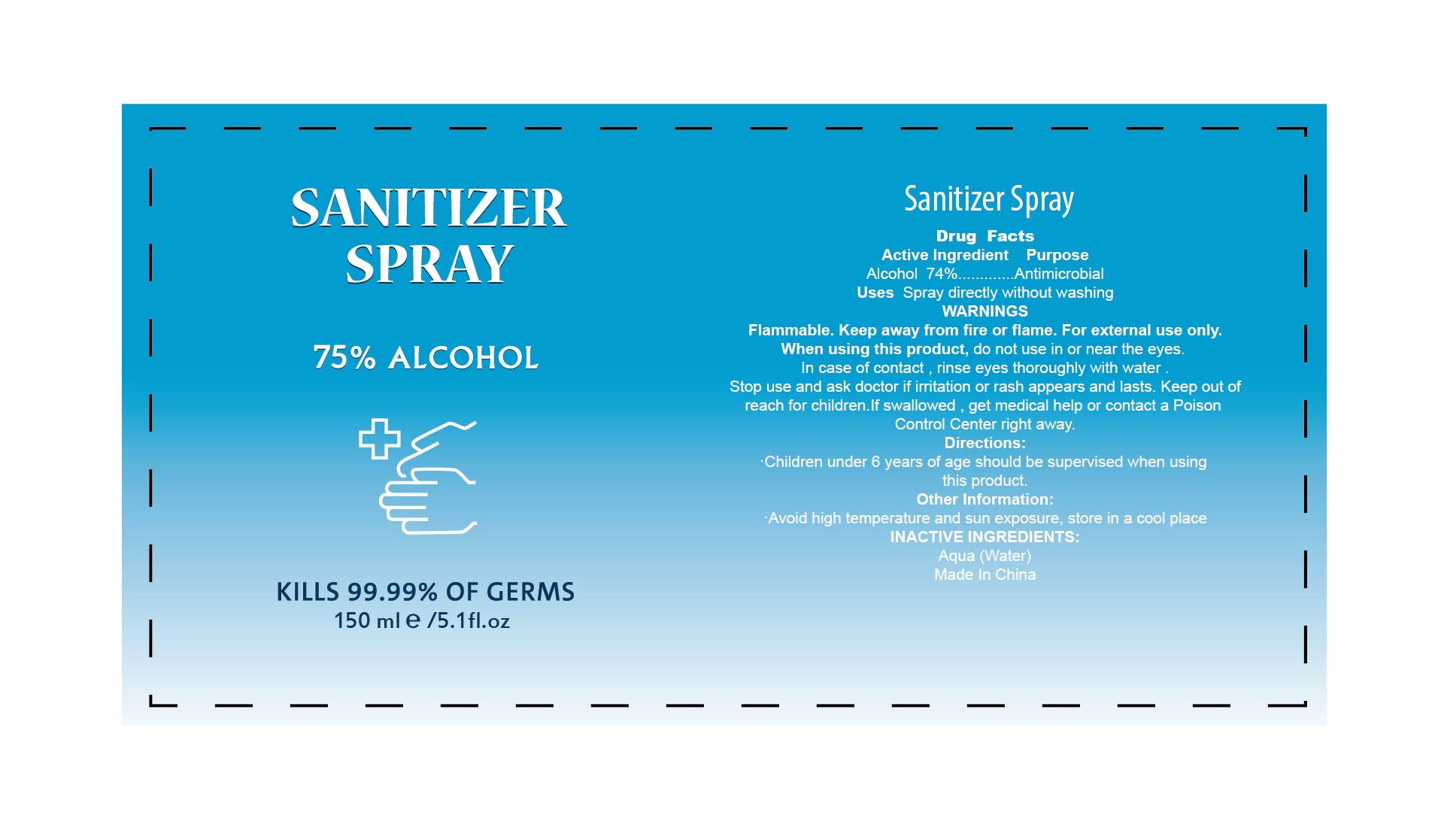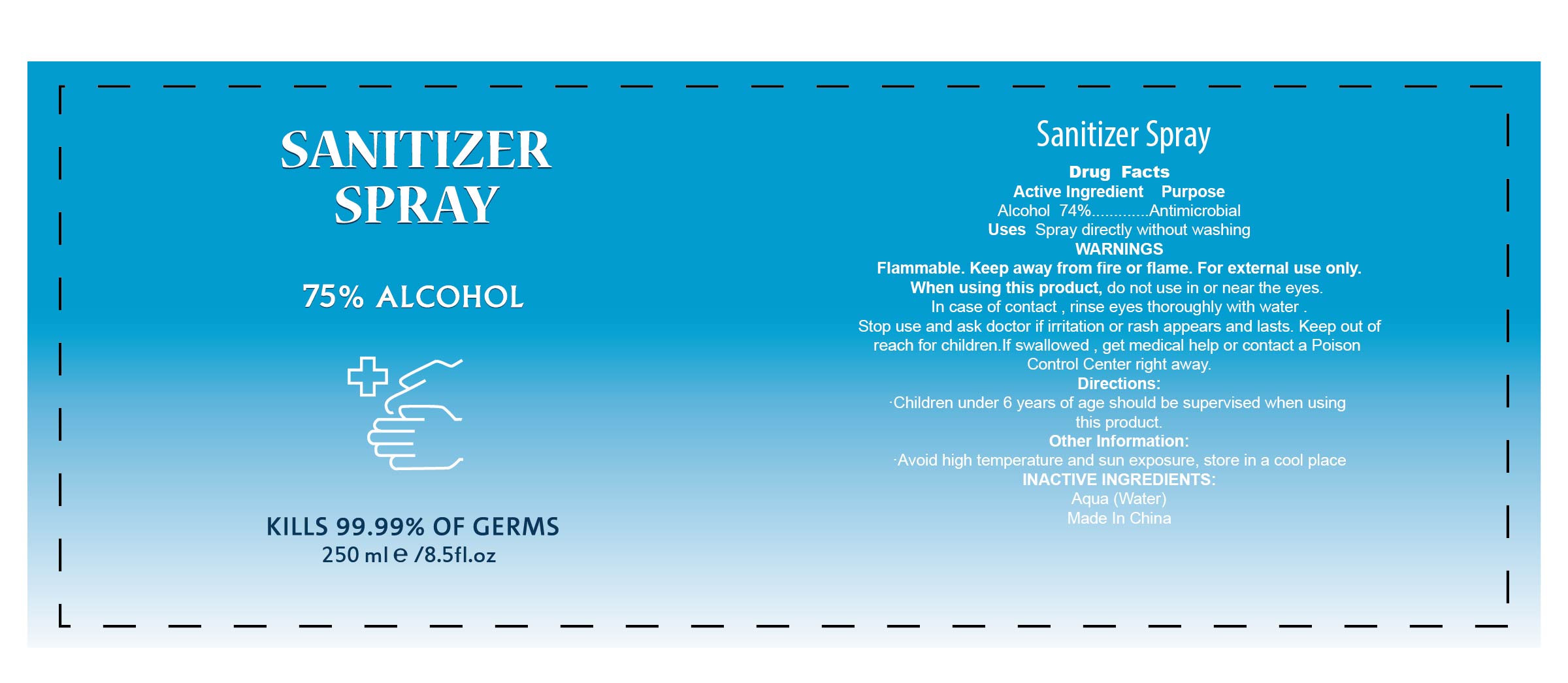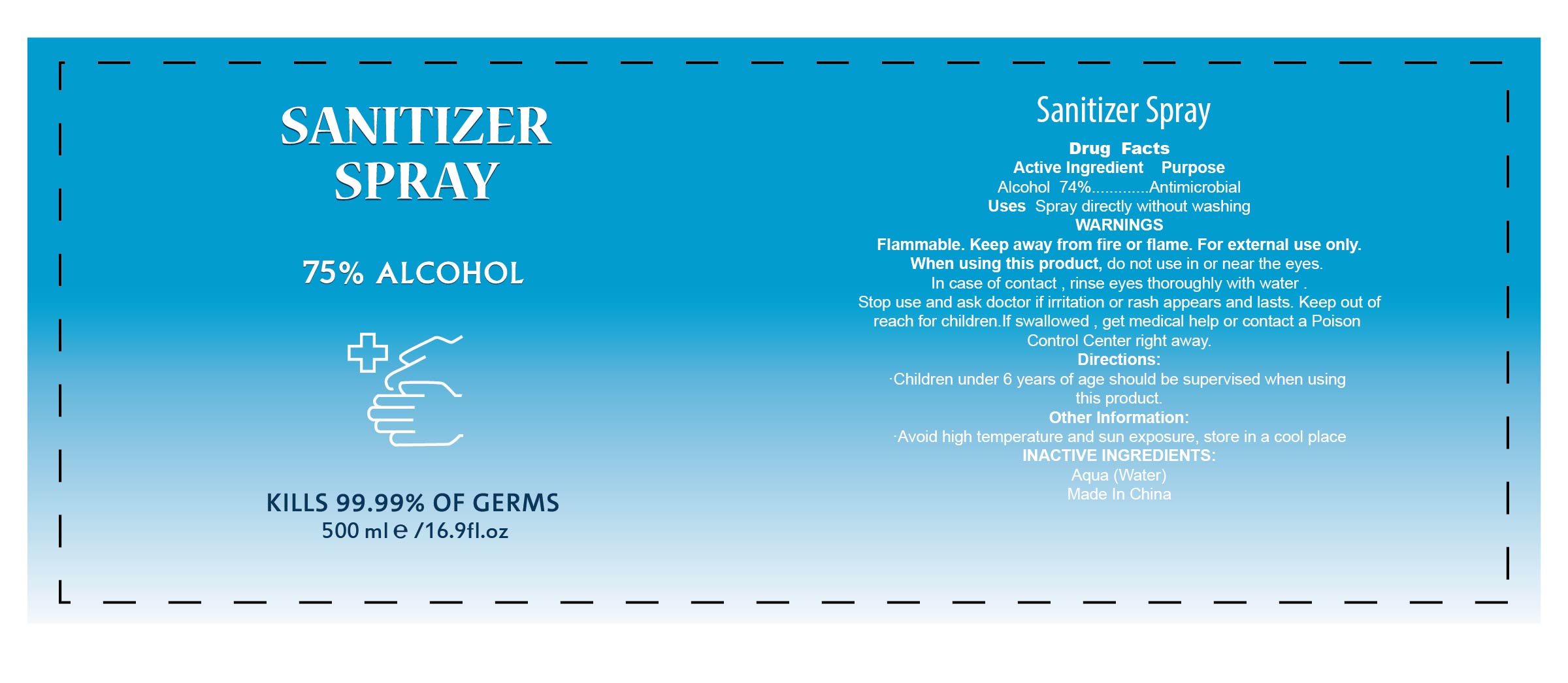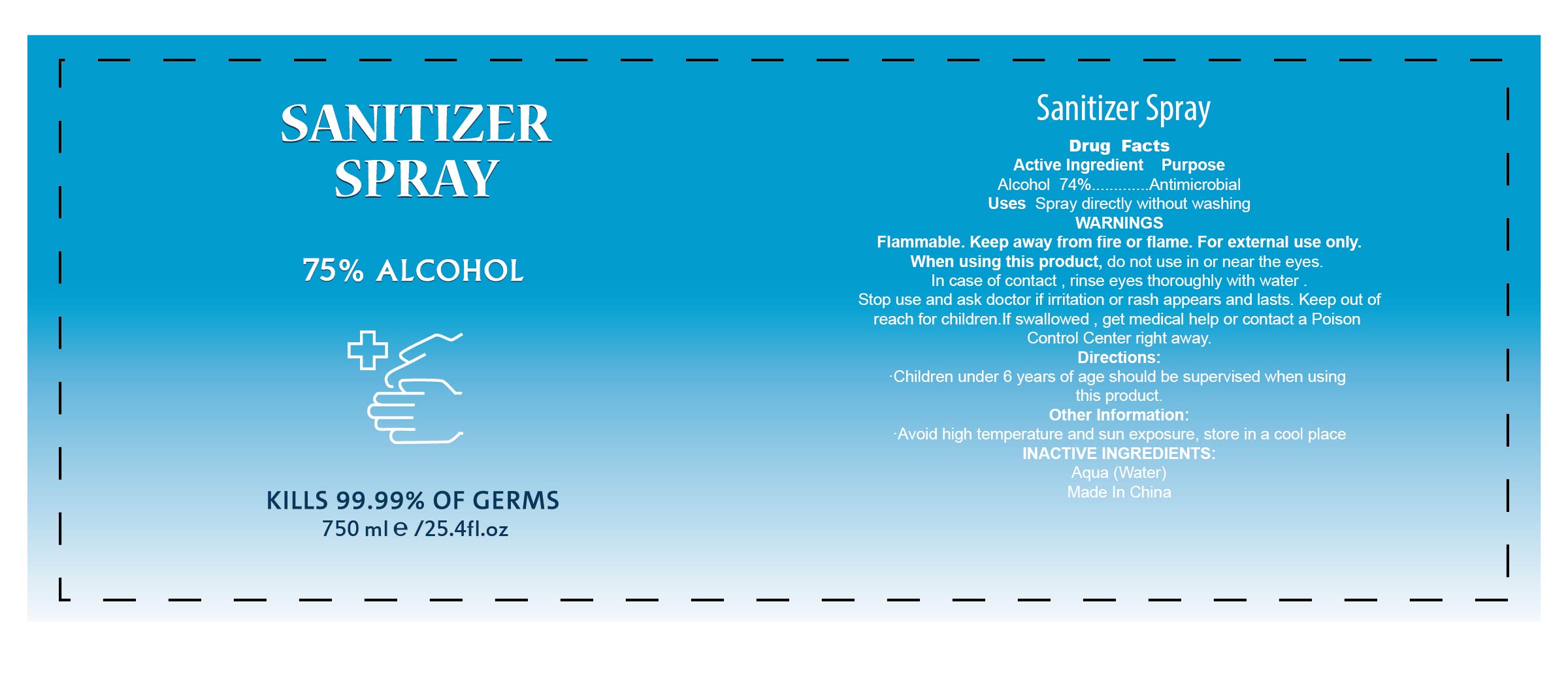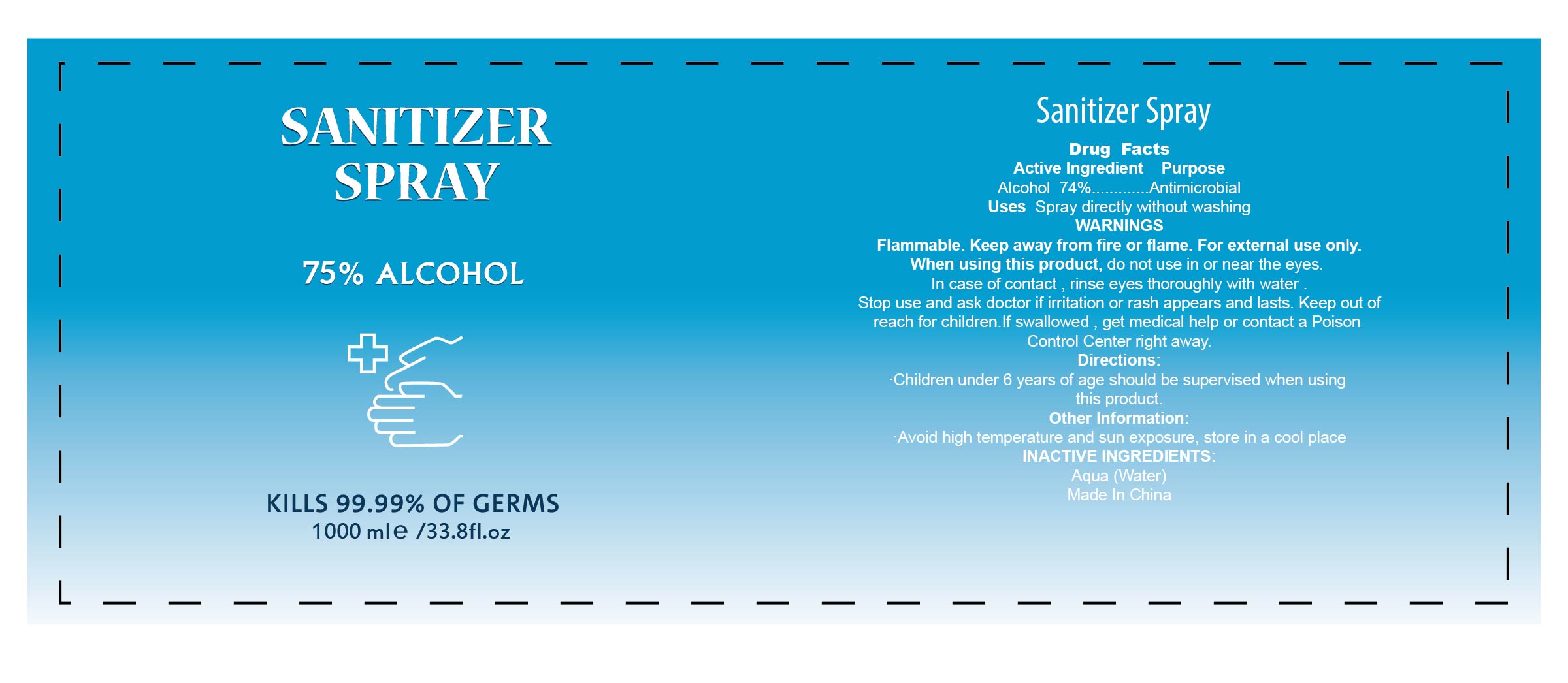 DRUG LABEL: S S
NDC: 74440-002 | Form: SPRAY
Manufacturer: Jiangxi Iris Chemical Co.,ltd
Category: otc | Type: HUMAN OTC DRUG LABEL
Date: 20200413

ACTIVE INGREDIENTS: ALCOHOL 74 mL/100 mL
INACTIVE INGREDIENTS: WATER

SANITIZER SPRAY

Active Ingredient

Alcohol 74%

Purpose

Antimicrobial

Uses

Spray directly without washing

WARNINGS

Flammable.Keep away from fire or flame.For external use only.

When using this product

do not use in or near the eyes.

In case of contact,rinse eyes thoroughly with water.

Stop use and ask doctor if irritation or rash appears and lasts.Keep out of reach for children.If swallowed, get medical help or contact a Poison Control Center right away.

Directions

Children under 6 years of age should be supervised when using this product.

Other Information

Avoid high temperature and sun exposure,store in a cool place

INACTIVE INGREDIENTS

Aqua(Water)